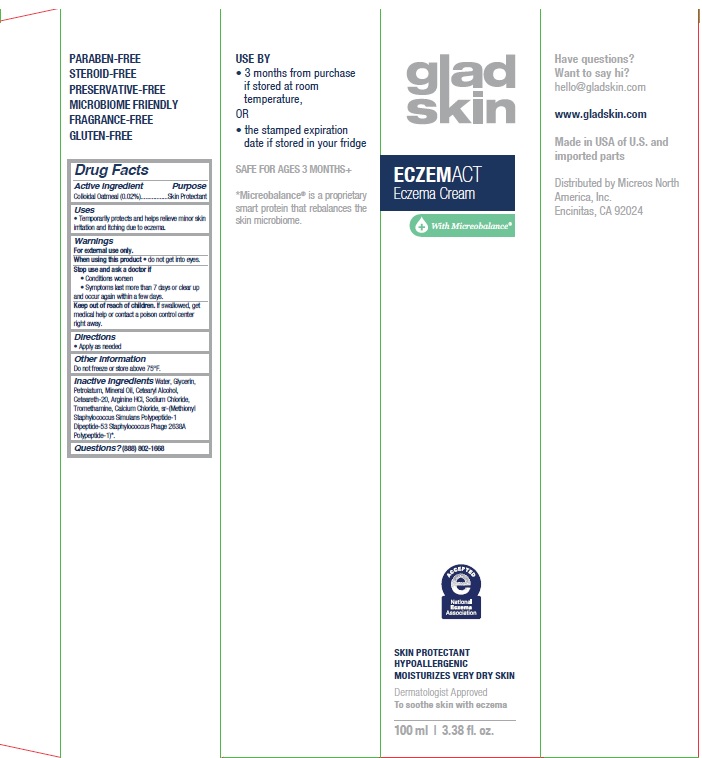 DRUG LABEL: GLADSKIN ECZEMACT ECZEMA
NDC: 73105-003 | Form: CREAM
Manufacturer: Micreos North America, Inc.
Category: otc | Type: HUMAN OTC DRUG LABEL
Date: 20260225

ACTIVE INGREDIENTS: OATMEAL 0.2 mg/1 mL
INACTIVE INGREDIENTS: WATER; GLYCERIN; PETROLATUM; CETOSTEARYL ALCOHOL; MINERAL OIL; ARGININE HYDROCHLORIDE; SODIUM CHLORIDE; POLYOXYL 20 CETOSTEARYL ETHER; TROMETHAMINE; CALCIUM CHLORIDE

GLADSKIN ECZEMACT ECZEMA CREAM

Active Ingredient

Colloidal Oatmeal (0.02%)

Purpose

Skin Protectant

Uses

Temporarily protects and helps relieve minor skin irritation and itching due to eczema.

Warnings

For external use only.

When using this product do not get into eyes.

Stop use and ask a doctor if:

- Conditions worsen
- Symptoms last more than 7 days or clear up and occur again within a few days.

Keep out of reach of children. If swallowed, get medical help or contact a poison control center right away.

Directions

- Apply as needed

Inactive Ingredients

Water, Glycerin, Petrolatum, Mineral Oil, Cetearyl Alcohol, Ceteareth-20, Arginine HCl, Sodium Chloride, Tromethamine, Calcium Chloride, sr-(Methionyl Staphylococcus Simulans Polypeptide-1 Dipeptide-53 Staphylococcus Phage 2638A Polypeptide-1)*

*Micreobalance™ is a proprietary smart protein that rebalances the skin microbiome.

Questions?

(888) 802-1668

Company Information

Distributed by Micreos North America, Inc. Encinitas, CA 92024

gladskin.com